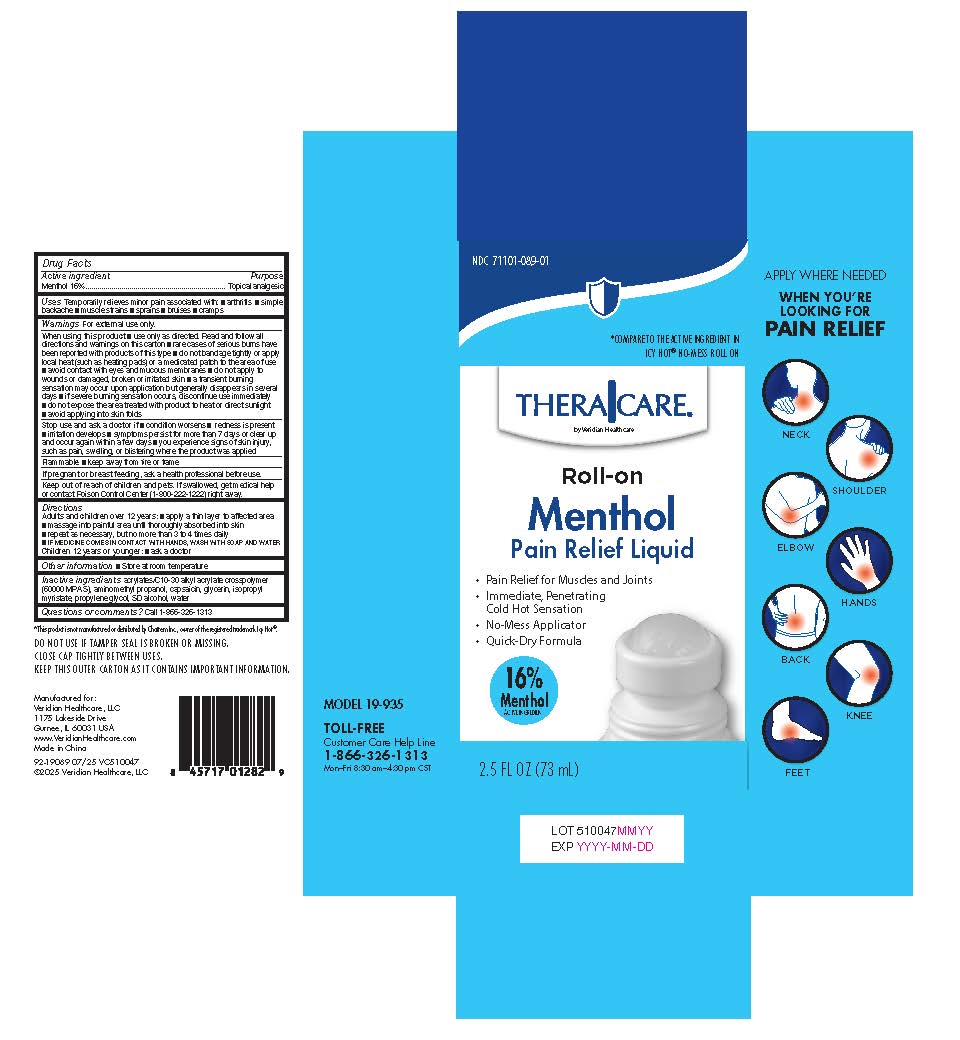 DRUG LABEL: TheraCare Roll-on Menthol 16% Pain Relief Liquid
NDC: 71101-089 | Form: LIQUID
Manufacturer: Veridian Healthcare
Category: otc | Type: HUMAN OTC DRUG LABEL
Date: 20250922

ACTIVE INGREDIENTS: MENTHOL 0.16 g/1 mL
INACTIVE INGREDIENTS: CAPSAICIN; GLYCERIN; ISOPROPYL MYRISTATE; PROPYLENE GLYCOL; ALCOHOL; AMINOMETHYL PROPANOL; WATER; ACRYLATES/C10-30 ALKYL ACRYLATE CROSSPOLYMER (60000 MPA.S)

TheraCare Roll-on Menthol 16% Pain Relief Liquid

TheraCare Roll-on Menthol 16% Pain Relief Liquid

Active ingredient

Menthol 16%

Purpose

Topical analgesic

Uses

temporarily relieves minor pain associated with:

- arthritis
- simple backache
- muscle strains
- sprains
- bruises
- cramps

Warnings

For external use only

When using this product

- use only as directed. Read and follow all directions and warnings on this carton.
- avoid contact with eyes and mucous membranes
- rare cases of serious burns have been reported with products of this type
- do not apply to wounds or damaged, broken or irritated skin
- do not bandage tightly or apply local heat (such as heating pads) or a medicated patch to the area of use
- a transient burning sensation may occur upon application but generally disappears in several days
- if severe burning sensation occurs, discontinue use immediately
- do not expose the area treated with product to heat or direct sunlight
- avoid applying into skin folds

Stop use and ask a doctor if

- condition worsens
- redness is present
- irritation develops
- symptoms persist for more than 7 days or clear up and occur again within a few days
- you experience signs of skin injury, such as pain, swelling, or blistering where the product was applied

Flammable■ Keep away from fire or flame

If pregnant or breast-feeding,

ask a health professional before use.

Keep out of reach of children.

If swallowed, get medical help or contact a Poison Control Center (1-800-222-1222) right away.

Directions

adults and children over 12 years:

- apply a thin layer to affected area
- massage into painful area until thoroughly absorbed into skin
- repeat as necessary, but no more than 3 to 4 times daily
- IF MEDICINE COMES IN CONTACT WITH HANDS, WASH WITH SOAP AND WATER

children 12 years or younger:ask a doctor

Inactive ingredients

acrylates/C10-30 alkyl acrylate crosspolymer(60000 MPA.S), aminomethyl propanol, capsaicin, glycerin, isopropyl

myristate, propylene glycol, SD alcohol, water